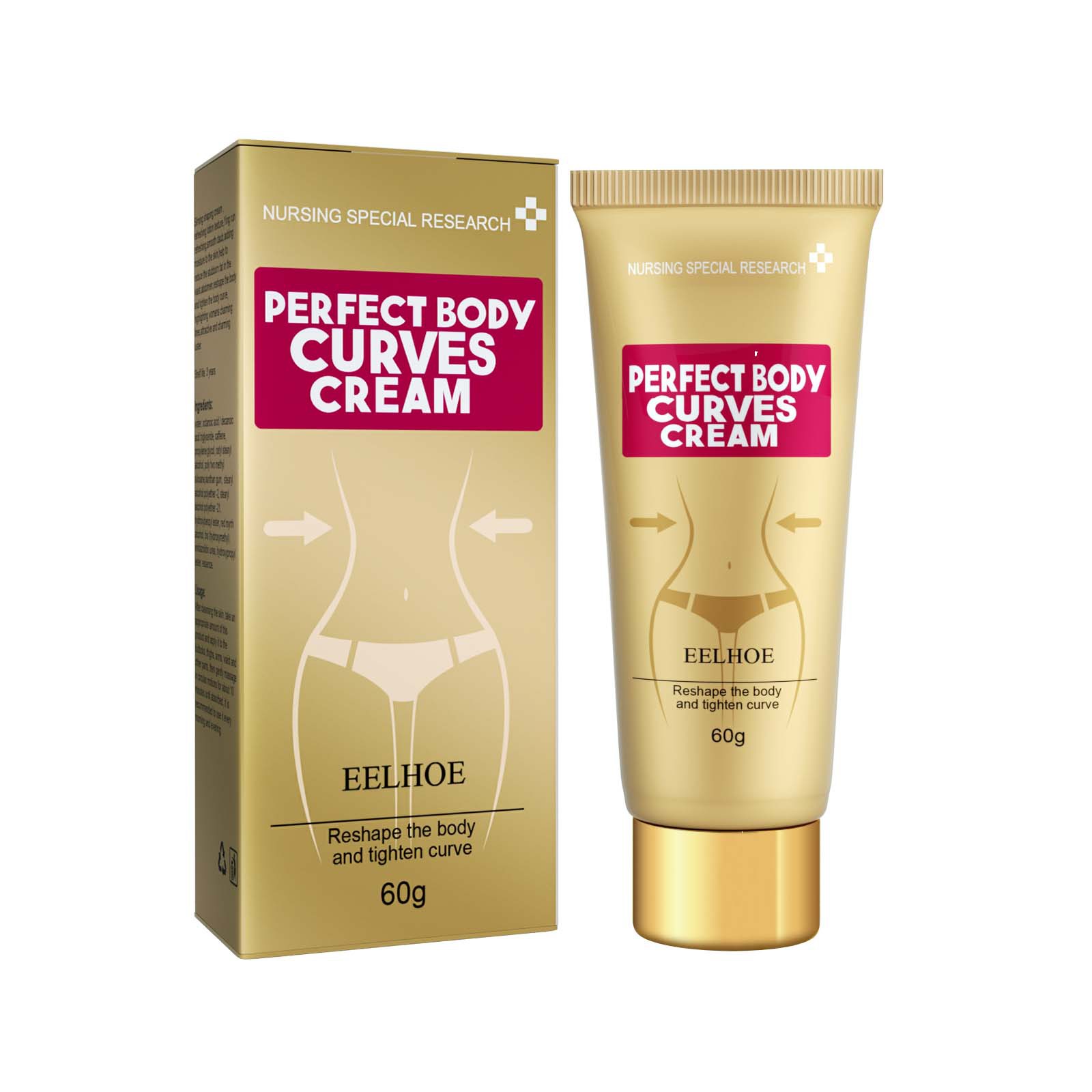 DRUG LABEL: Perfect Body Curves Cream
NDC: 83675-023 | Form: CREAM
Manufacturer: Guangzhou Hanhai Trading Co., Ltd
Category: otc | Type: HUMAN OTC DRUG LABEL
Date: 20231008

ACTIVE INGREDIENTS: GINGER 25 g/100 g
INACTIVE INGREDIENTS: CENTELLA ASIATICA; MANGO

Active Ingredient

Ginger 25.0%

Purpose

Slimming

Use

Eliminate edema
Tighten the arm
Slender and smooth

Warnings

For external use only. Do not take it internally.

Keep Out Of Reach Of Children
Sensitive Skin

Do not use

Product shall not be eat

When Using

Apply the product to the part you need.

Stop Use

In case of adverse reactions, please stop using this product.If the symptoms.

Ask Doctor

ask doctor in case of Sensitive Skin

Keep Oot Of Reach Of Children

Directions

Apply the product to the part you need.

Other information

Store the product in a cool, dry and well-ventilated place

Avoid direct sunlight

Inactive ingredients

Mango

Centella Asiatica